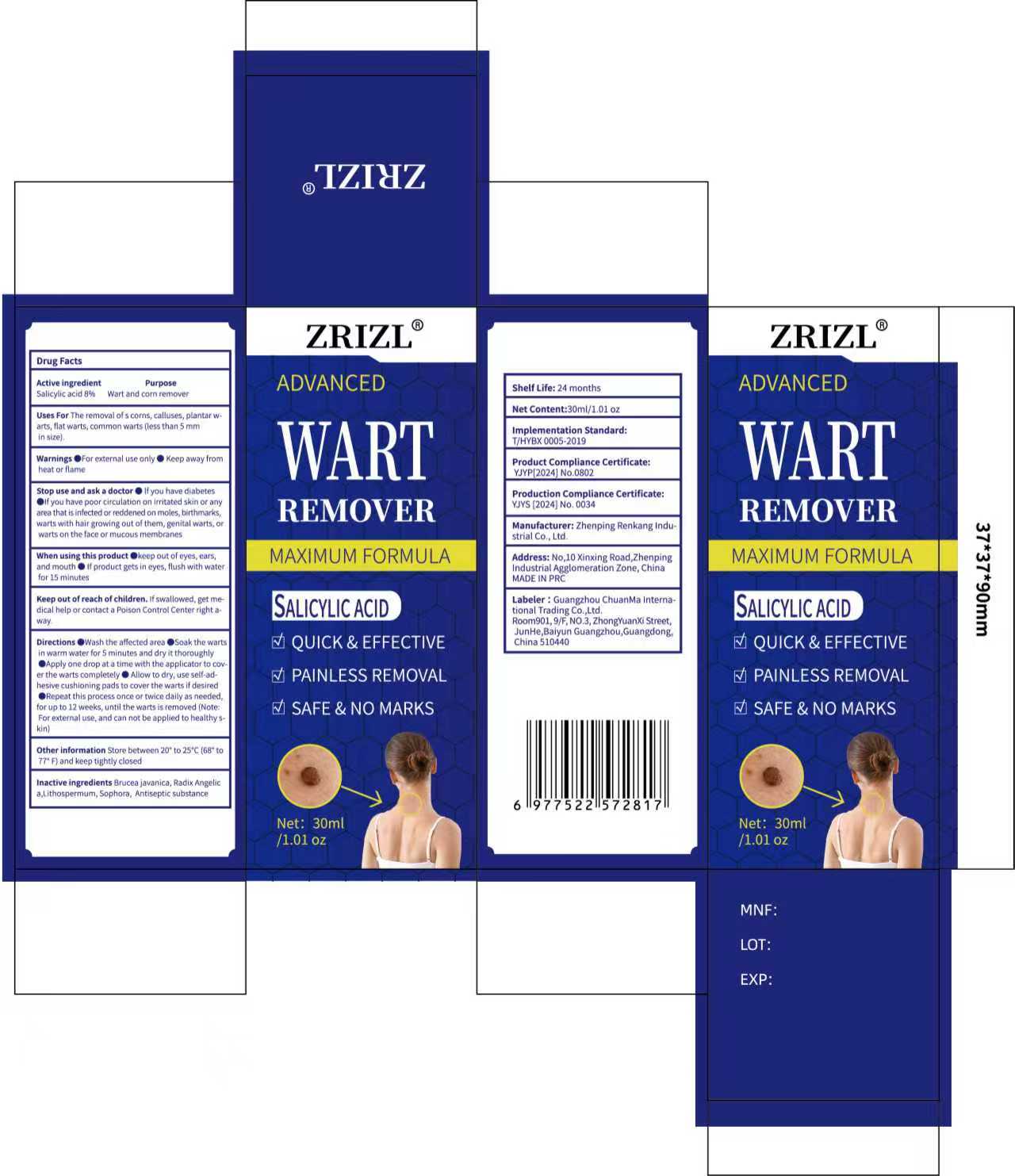 DRUG LABEL: ZRIZ wart Remover
NDC: 85593-014 | Form: LIQUID
Manufacturer: Guangzhou ChuanMa International Trading Co.,Ltd.
Category: otc | Type: HUMAN OTC DRUG LABEL
Date: 20250908

ACTIVE INGREDIENTS: SALICYLIC ACID 8 g/100 mL
INACTIVE INGREDIENTS: ALCOHOL; SOPHORA FLAVESCENS ROOT; LITHOSPERMUM INCISUM WHOLE; ANGELICA DAHURICA VAR. FORMOSANA WHOLE; BRUCEA JAVANICA WHOLE

Active ingredrents

Salicylic acid 8% w/w

PURPOSE

Uses For The removai ol s corns, calluses, piantar warts, filat warts, comman warts (less than 5 mmin stze).

WARNINGS

Warnings o For exernal use only e Keep away fromheat or flame

KEEP OUT OF REACH OF CHILDREN

Keep out of reach ofchildren, lfswallowed, get medical help or contact a Poison controt center right a-way

INDICATIONS AND USAGE

Directlons @Wash the affected area osoak the.wartsin warm water for $ minutes aind dry it thoroughly@Apply one drop at a time with the applicator to cov,er the warts completely m, Allow to dry, use self-adhesive cushloning pads to cover the warts if deslredeRepeat this process once or twice dally as neededfor up to 12 weeks, untll the warts is removed (Ncte.For external use, and can not be applied to healthy Skin)

INACTIVE INGREDIENT

Brucea javanica, Radix Angelica,Lithospermum, Sophora, Antiseptic substance

DOSAGE AND ADMINISTRATION

Repeat this process once or rwice dally as neededfor up to 12 weeks, untll the warts is remowed

OTHER SAFETY INFORMATION

lf you have diabetes if you have poor circulatlon on lrrltated skin or anyarea that isinfected or reddened on moles, birhmarks